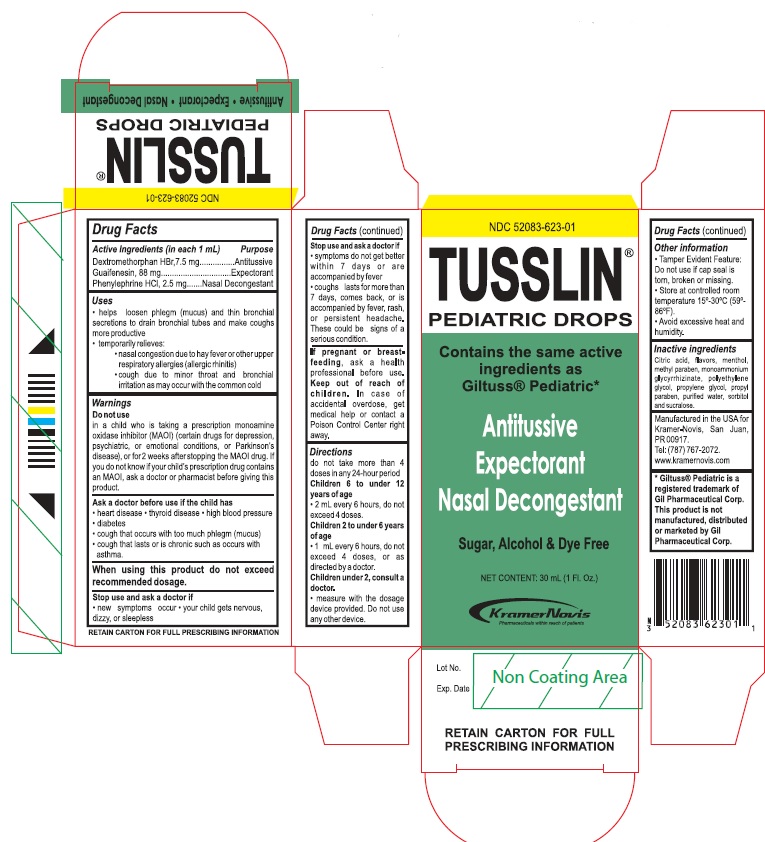 DRUG LABEL: Tusslin
NDC: 52083-623 | Form: SOLUTION/ DROPS
Manufacturer: Kramer Novis
Category: otc | Type: HUMAN OTC DRUG LABEL
Date: 20190916

ACTIVE INGREDIENTS: DEXTROMETHORPHAN HYDROBROMIDE 7.5 mg/1 mL; GUAIFENESIN 88 mg/1 mL; PHENYLEPHRINE HYDROCHLORIDE 2.5 mg/1 mL
INACTIVE INGREDIENTS: CITRIC ACID MONOHYDRATE; METHYLPARABEN; AMMONIUM GLYCYRRHIZATE; POLYETHYLENE GLYCOL, UNSPECIFIED; PROPYLENE GLYCOL; PROPYLPARABEN; WATER; SORBITOL; SUCRALOSE

Drug Facts

Active Ingredients (in each 1 mL) Purpose

Dextromethorphan HBr, 7.5 mg..............................Antitussive

Guaifenesin, 88 mg..............................................Expectorant

Phenylephrine HCl, 2.5 mg................................Nasal decongestant

Uses

- helps loosen phlegm (mucus) and thin bronchial secretions to drain bronchial tubes and make coughs more productive

- temporarily relieves:
- nasal congestion due to the common cold
- cough due to minor throat and bronchial irritation as may occur with the common cold

Warnings

Do not use
in child who is taking a prescription monoamine oxidase inhibitor (MAOI) (certain drugs for depression, psychiatric, or emotional conditions, or Parkinson’s disease), or for 2 weeks after stopping the MAOI drug. If you do not know if your child's prescription drug contains a MAOI, ask a doctor or pharmacist before giving this product.

Ask a doctor before use if your child has

- heart disease
- thyroid disease
- high blood pressure
- diabetes
- a cough that occurs with too much phlegm (mucus)
- cough that lasts or is chronic such as occurs with asthma

When using this product do not exceed recommended dosage
Stop use and ask a doctor if

- new symptoms occur
- your child gets nervous, dizzy or sleepless
- symptoms do not get better within 7 days or are accompanied by fever
- cough last more than 7 days, comes back, or is accompanied by fever, rash or persistent headache. These could be a signs of a serious condition.

PREGNANCY OR BREAST FEEDING

If pregnant or breast-feeding, ask a health professional before use.

Keep out of reach of children. In case of accidental overdose, get medical help or contact a Poison Control Center right away.

Directions

do not use more than 4 doses in any 24-hour period

Children 6 to under 12 years of age

- 2 mL every 6 hours, do not exceed 4 doses.

Children 2 to under 6 years of age

- 1 mL every 6 hours, do not exceed 4 doses, or as directed by a doctor.

Children under 2, consult a doctor

- measure with the dosage device provided. Do not use any other device.

Other information

Tamper Evident Feature: Do not use if cap seal is torn, broken or missing.

Store at controlled room temperature 15-30°C (59-86°F).

Avoid excessive heat and humidity.

INACTIVE INGREDIENT

Inactive ingredients Citric acid, flavors, menthol, methyl paraben, monoammonium glycyrrhizinate, polyethylene glycol, propylene glycol, propyl paraben, purified water, sorbitol and sucralose.

QUESTIONS

Manufactured in the USA for Kramer-Novis, San Juan, PR 00917.
Tel: (787) 767-2072
www.kramernovis.com

Principal Display Panel

TUSSLIN®

PEDIATRIC DROPS

Contains the same active ingredients as Glituss® Pediatric

Antitussive

Expectorant

Nasal Decongestant

Sugar, Alcohol & Dye Free

NET CONTENT: 30 mL (1 Fl. Oz.)

KRAMER-NOVIS